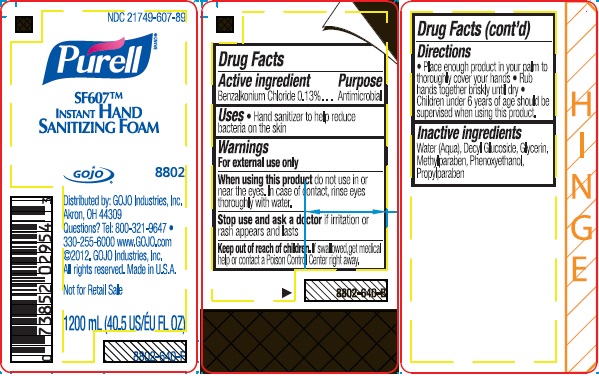 DRUG LABEL: PURELL SF607 Instant Hand Sanitizing
NDC: 21749-607 | Form: LIQUID
Manufacturer: GOJO Industries, Inc.
Category: otc | Type: HUMAN OTC DRUG LABEL
Date: 20241216

ACTIVE INGREDIENTS: BENZALKONIUM CHLORIDE 0.13 mg/100 mL
INACTIVE INGREDIENTS: WATER; GLYCERIN; METHYLPARABEN; PHENOXYETHANOL

PURELL SF607 Instant Hand Sanitizing Foam

Active Ingredient

Benzalkonium Chloride 0.13%

Purpose

Antimicrobial

Use

- Hand sanitizer to help reduce bacteria on the skin

Warnings

For external use only

WHEN USING

When using this productdo not use in or near the eyes. In case of contact, rinse eyes thoroughly with water.

Stop use and ask a doctor ifirritation or rash appears and lasts

Keep out of reach of children. If swallowed, get medical help or contact a Poison Control Center right away

Directions

- Place enough product in your palm to thoroughly cover your hands
- Rub hands together briskly until dry
- Children under 6 years of age should be supervised when using this product.

INACTIVE INGREDIENT

Water (Aqua), Decyl Glucoside, Glycerin, Methylparaben, Phenoxyethanol, Propylparaben